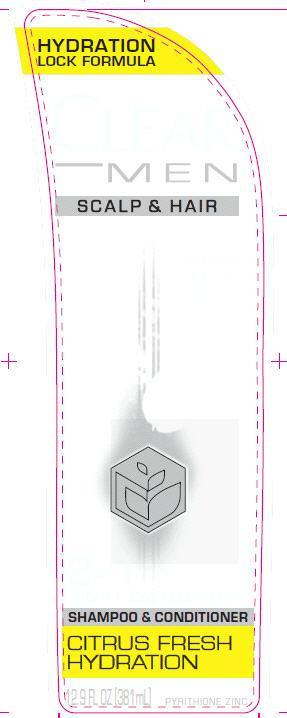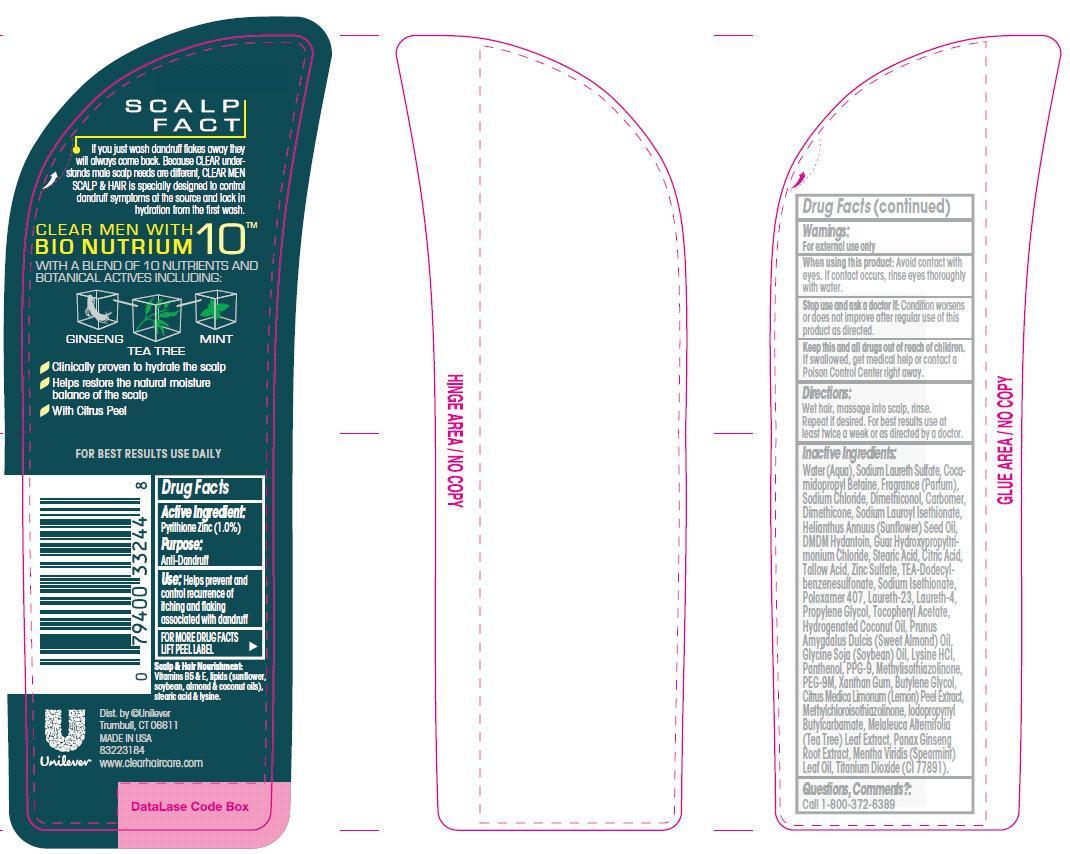 DRUG LABEL: Clear
NDC: 64942-1313 | Form: SHAMPOO
Manufacturer: Conopco Inc. d/b/a Unilever
Category: otc | Type: HUMAN OTC DRUG LABEL
Date: 20130926

ACTIVE INGREDIENTS: Pyrithione Zinc 1.0 g/100 mL
INACTIVE INGREDIENTS: WATER; SODIUM LAURETH SULFATE; COCAMIDOPROPYL BETAINE; SODIUM CHLORIDE; TITANIUM DIOXIDE; SODIUM LAUROYL ISETHIONATE; DMDM HYDANTOIN; TRIETHANOLAMINE DODECYLBENZENESULFONATE; SUNFLOWER OIL; CITRIC ACID MONOHYDRATE; PPG-9; METHYLCHLOROISOTHIAZOLINONE; METHYLISOTHIAZOLINONE; SPEARMINT OIL; GUAR HYDROXYPROPYLTRIMONIUM CHLORIDE (1.7 SUBSTITUENTS PER SACCHARIDE); STEARIC ACID; ZINC SULFATE; DIMETHICONOL (41 MPA.S); DIMETHICONE; SODIUM ISETHIONATE; POLOXAMER 407; LAURETH-23; LAURETH-4; .ALPHA.-TOCOPHEROL ACETATE, D-; ALMOND OIL; POLYETHYLENE GLYCOL 400000; PANTHENOL; LYSINE HYDROCHLORIDE; HYDROGENATED COCONUT OIL; SOYBEAN OIL; XANTHAN GUM; ASIAN GINSENG; TEA TREE OIL; BUTYLENE GLYCOL; IODOPROPYNYL BUTYLCARBAMATE; PROPYLENE GLYCOL; LEMON PEEL

Clear Men Citrus Fresh Hydration Anti Dandruff Shampoo and Conditioner

Active Ingredient:

Pyrithione Zinc (1.0%)

Purpose:

Anti-Dandruff

INDICATIONS AND USAGE

Use: helps prevent and control recurrence of itching and flaking associated with dandruff

Warnings:
For external use only

When using this product: avoid contact with eyes. If contact occurs, rinse eyes thoroughly with water.

Stop use and ask a doctor if: Condition worsens or does not improve after regular use of this product as directed.

KEEP OUT OF REACH OF CHILDREN

Keep this and all drugs out of reach of children. If swallowed, get medical help or contact a Poison Control Center right away.

Directions:

Wet hair, massage into scalp, rinse. Repeat if desired. For best results use at least twice a week or as directed by a doctor.

Inactive Ingredients:

Water (Aqua), Sodium Laureth Sulfate, Cocamidopropyl Betaine, Fragrance (Parfum), Sodium Chloride, Dimethiconol, Carbomer, Dimethicone, Sodium Lauroyl Isethionate, Helianthus Annuus (Sunflower) Seed Oil, DMDM Hydantoin, Guar Hydroxypropyltrimonium Chloride, Stearic Acid, Citric Acid, Tallow Acid, Zinc Sulfate, TEA-Dodecylbenzenesulfonate, Sodium Isethionate, Poloxamer 407, Laureth-23, Laureth-4, Propylene Glycol, Tocopheryl Acetate, Hydrogenated Coconut Oil, Prunus Amygdalus Dulcis (Sweet Almond) Oil, Glycine Soja (Soybean) Oil, Lysine HCl, Panthenol, PPG-9, Methylisothiazolinone, PEG-9M, Xanthan Gum, Butylene Glycol, Citrus Medica Limonum (Lemon) Peel Extract, Methylchloroisothiazolinone, Iodopropynyl Butylcarbamate, Melaleuca Alternifolia (Tea Tree) Leaf Extract, Panax Ginseng Root Extract, Mentha Viridis (Spearmint) Leaf Oil, Titanium Dioxide (CI 77891)

Questions, comments?: 1-800-372-6389